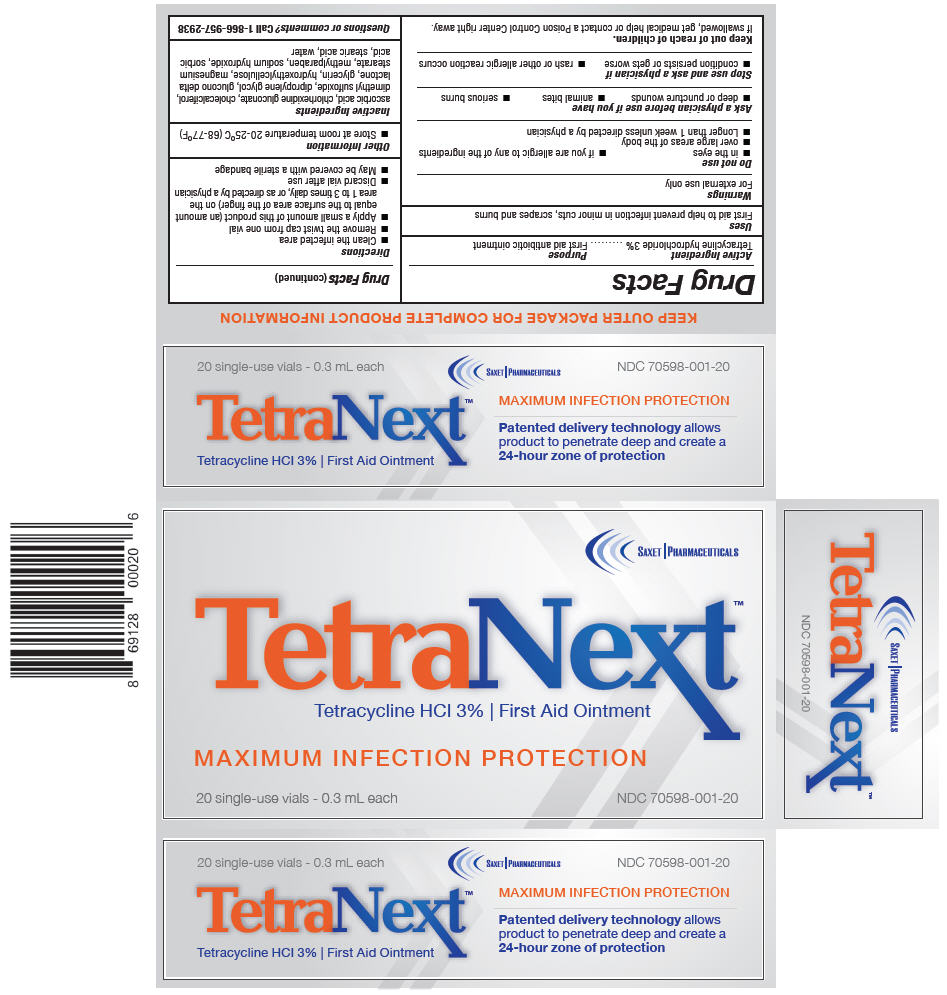 DRUG LABEL: TetraNext
NDC: 70598-001 | Form: OINTMENT
Manufacturer: Saxet Pharmaceuticals
Category: otc | Type: HUMAN OTC DRUG LABEL
Date: 20170203

ACTIVE INGREDIENTS: Tetracycline Hydrochloride 30 mg/1 mL
INACTIVE INGREDIENTS: Water; glycerin; hydroxymethyl cellulose; chlorhexidine gluconate; gluconolactone; methylparaben; sodium hydroxide; dipropylene glycol; dimethyl sulfoxide; sorbic acid; ascorbic acid; magnesium stearate; stearic acid

TetraNext™

Drug Facts

Active Ingredient

Tetracycline hydrochloride 3%

Purpose

First aid antibiotic ointment

Uses

First aid to help prevent infection in minor cuts, scrapes and burns

Warnings

For external use only

Do not use

- in the eyes
- if you are allergic to any of the ingredients
- over large areas of the body
- Longer than 1 week unless directed by a physician

Ask a physician before use if you have

- deep or puncture wounds
- animal bites
- serious burns

Stop use and ask a physician if

- condition persists or gets worse
- rash or other allergic reaction occurs

Keep out of reach of children.

If swallowed, get medical help or contact a Poison Control Center right away.

Directions

- Clean the infected area
- Remove the twist cap from one vial
- Apply a small amount of this product (an amount equal to the surface area of the finger) on the area 1 to 3 times daily, or as directed by a physician
- Discard vial after use
- May be covered with a sterile bandage

Other Information

- Store at room temperature 20-25°C (68-77°F)

Inactive Ingredients

Water, glycerin, hydroxethylcellulose, chlor-hexide gluconate, glucono delta lactone, methylparaben, sodium hydroxide, dipropylene glycol, dimethyl sulfoxide, sorbic acid, ascorbic acid, magnesium stearate, stearic acid

Questions or comments?

Call 1-866-957-2938

PRINCIPAL DISPLAY PANEL - 0.3 mL Vial Carton

SAXET | PHARMACEUTICALS

TetraNext™

Tetracycline HCl 3% | First Aid Ointment

MAXIMUM INFECTION PROTECTION

20 single-use vials - 0.3 mL each
NDC 70598-001-20